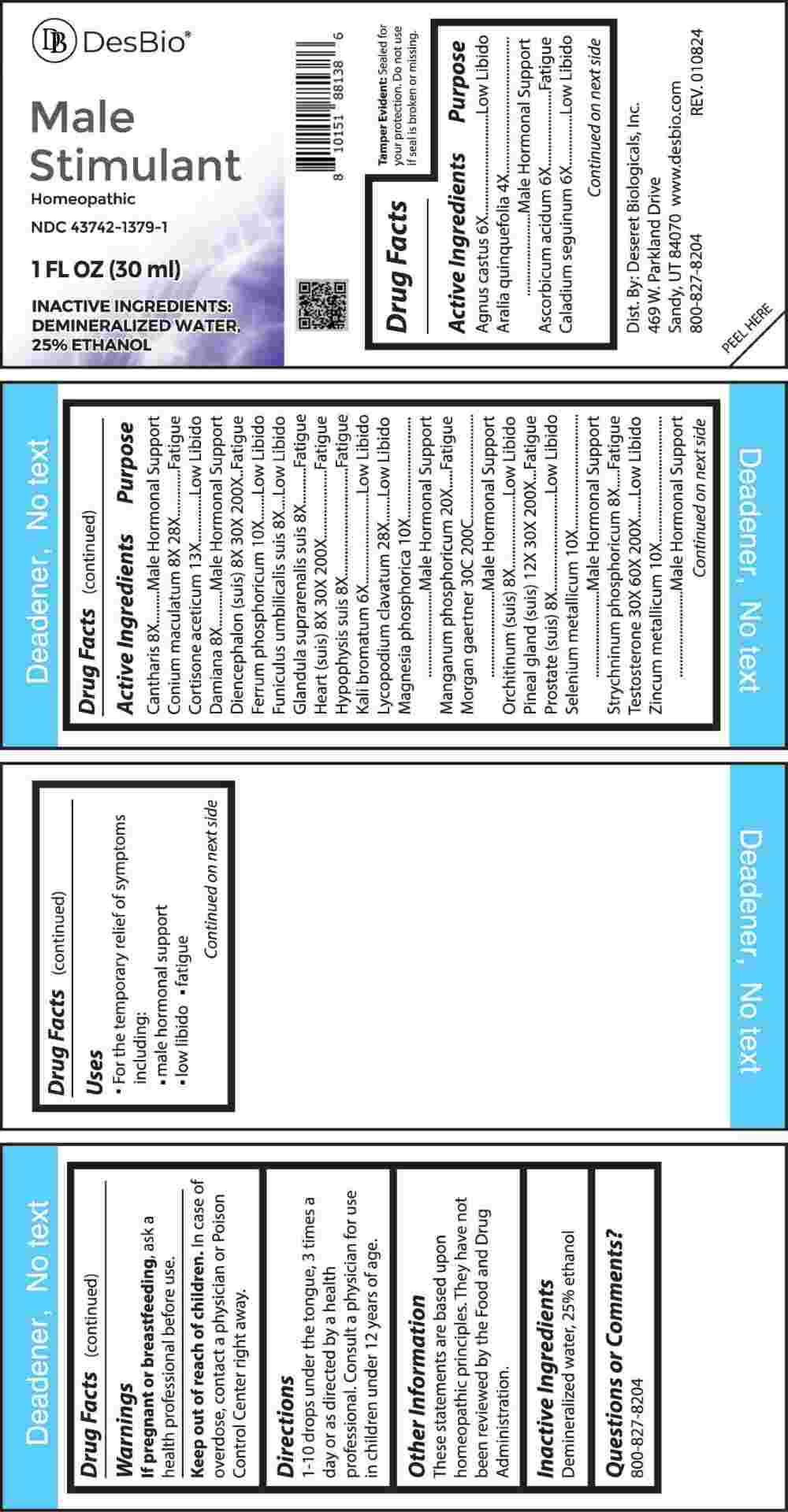 DRUG LABEL: Male Stimulant
NDC: 43742-1379 | Form: LIQUID
Manufacturer: Deseret Biologicals, Inc.
Category: homeopathic | Type: HUMAN OTC DRUG LABEL
Date: 20240415
DEA Schedule: CIII

ACTIVE INGREDIENTS: AMERICAN GINSENG 4 [hp_X]/1 mL; CHASTE TREE FRUIT 6 [hp_X]/1 mL; ASCORBIC ACID 6 [hp_X]/1 mL; DIEFFENBACHIA SEGUINE WHOLE 6 [hp_X]/1 mL; POTASSIUM BROMIDE 6 [hp_X]/1 mL; LYTTA VESICATORIA 8 [hp_X]/1 mL; TURNERA DIFFUSA LEAFY TWIG 8 [hp_X]/1 mL; SUS SCROFA UMBILICAL CORD 8 [hp_X]/1 mL; SUS SCROFA ADRENAL GLAND 8 [hp_X]/1 mL; SUS SCROFA PITUITARY GLAND 8 [hp_X]/1 mL; SUS SCROFA TESTICLE 8 [hp_X]/1 mL; SUS SCROFA PROSTATE 8 [hp_X]/1 mL; STRYCHNINE PHOSPHATE DIHYDRATE 8 [hp_X]/1 mL; CONIUM MACULATUM FLOWERING TOP 8 [hp_X]/1 mL; SUS SCROFA DIENCEPHALON 8 [hp_X]/1 mL; PORK HEART 8 [hp_X]/1 mL; FERROSOFERRIC PHOSPHATE 10 [hp_X]/1 mL; MAGNESIUM PHOSPHATE, DIBASIC TRIHYDRATE 10 [hp_X]/1 mL; SELENIUM 10 [hp_X]/1 mL; ZINC 10 [hp_X]/1 mL; SUS SCROFA PINEAL GLAND 12 [hp_X]/1 mL; CORTISONE ACETATE 13 [hp_X]/1 mL; MANGANESE PHOSPHATE, DIBASIC 20 [hp_X]/1 mL; LYCOPODIUM CLAVATUM SPORE 28 [hp_X]/1 mL; TESTOSTERONE 30 [hp_X]/1 mL; SALMONELLA ENTERICA SUBSP. ENTERICA SEROVAR ENTERITIDIS 30 [hp_C]/1 mL
INACTIVE INGREDIENTS: WATER; ALCOHOL

DRUG FACTS:

ACTIVE INGREDIENTS:

Agnus Castus 6X, Aralia Quinquefolia 4X, Ascorbicum Acidum 6X, Caladium Seguinum 6X, Cantharis 8X, Conium Maculatum 8X, Cortisone Aceticum 13X, Damiana 8X, Diencephalon (Suis) 8X, 30X, 200X, Ferrum Phosphoricum 10X, Funiculus Umbilicalis Suis 8X, Glandula Suprarenalis Suis 8X, Heart (Suis) 8X, 30X, 200X, Hypophysis Suis 8X, Kali Bromatum 6X, Lycopodium Clavatum 28X, Magnesia Phosphorica 10X, Manganum Phosphoricum 20X, Morgan Gaertner 30C, 200C, Orchitinum (Suis) 8X, Pineal Gland (Suis) 12X, 30X, 200X, Prostate (Suis) 8X, Selenium Metallicum 10X, Strychninum Phosphoricum 8X, 28X, Testosterone 30X, 60X, 200X, Zincum Metallicum 10X.

PURPOSE:

Agnus Castus – Low Libido, Aralia Quinquefolia – Male Hormonal Support, Ascorbicum Acidum - Fatigue, Caladium Seguinum – Low Libido, Cantharis – Male Hormonal Support, Conium Maculatum - Fatigue, Cortisone Aceticum – Low Libido, Damiana – Male Hormonal
Support, Diencephalon (Suis) - Fatigue, Ferrum Phosphoricum – Low Libido, Funiculus Umbilicalis Suis – Low Libido, Glandula Suprarenalis Suis - Fatigue, Heart (Suis) - Fatigue, Hypophysis Suis - Fatigue, Kali Bromatum – Low Libido, Lycopodium Clavatum – Low Libido, Magnesia Phosphorica – Male Hormonal Support, Manganum Phosphoricum - Fatigue, Morgan Gaertner – Male Hormonal Support, Orchitinum (Suis) – Low Libido, Pineal Gland (Suis) - Fatigue, Prostate (Suis) – Low Libido, Selenium Metallicum – Male Hormonal Support, Strychninum Phosphoricum - Fatigue, Testosterone – Low Libido, Zincum Metallicum – Male Hormonal Support

USES:

• For the temporary relief of symptoms including:

• male hormonal support • low libido • fatigue

These statements are based upon homeopathic principles. They have not been reviewed by the Food and Drug Administration.

WARNINGS:

If pregnant or breast-feeding, ask a health professional before use.

Keep out of reach of children. In case of overdose, contact a physician or Poison Control Center right away.

Tamper Evident: Sealed for your protection. Do not use if seal is broken or missing.

KEEP OUT OF REACH OF CHILDREN:

In case of overdose, contact a physician or Poison Control Center right away.

DIRECTIONS:

1-10 drops under the tongue, 3 times a day or as directed by a health professional. Consult a physician for use in children under 12 years of age.

INACTIVE INGREDIENTS:

Demineralized water, 25% ethanol

QUESTIONS:

Dist. By: Deseret Biologicals, Inc.
469 W. Parkland Drive
Sandy, UT 84070

www.desbio.com

800-827-8204

PACKAGE LABEL DISPLAY:

Des Bio

Male Stimulant

Homeopathic
NDC 43742-1379-1
1 FL OZ (30 ml)